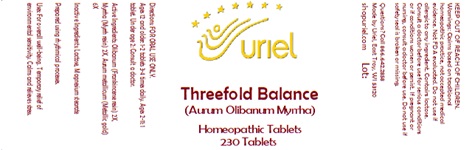 DRUG LABEL: Threefold Balance
NDC: 48951-9364 | Form: TABLET
Manufacturer: Uriel Pharmacy, Inc.
Category: homeopathic | Type: HUMAN OTC DRUG LABEL
Date: 20240924

ACTIVE INGREDIENTS: MYRRH 2 [hp_X]/1 1; GOLD 6 [hp_X]/1 1; FRANKINCENSE 2 [hp_X]/1 1
INACTIVE INGREDIENTS: LACTOSE, UNSPECIFIED FORM; MAGNESIUM STEARATE

Threefold Balance

INDICATIONS AND USAGE

Directions: FOR ORAL USE ONLY.

DOSAGE AND ADMINISTRATION

Ages 12 and older: 1-2 tablets 3-4 times daily. Ages 2-11: 1 tablet. Under age 2: Consult a doctor.

ACTIVE INGREDIENT

Active Ingredients: Olibanum (Rubber resin from wood of incense tree) 2X, Myrrha (Myrrh resin) 2X, Aurum metallicum (Metallic gold) 6X

Inactive Ingredients: Lactose, Magnesium stearate

Prepared using rhythmical processes

PURPOSE

Uses: For overall well-being. Temporary relief of environmental sensitivity. Calms and relieves stress.

KEEP OUT OF REACH OF CHILDREN.

WARNINGS

Warnings: Claims based on traditional homeopathic practice, not accepted medical evidence. Not FDA evaluated. Do not use if allergic to any ingredient. Contains lactose. Consult a doctor before use for serious conditions or if conditions worsen or persist. If pregnant or nursing, consult a doctor before use. Do not use if safety seal is broken or missing.

Questions? Call 866.642.2858
Made by Uriel, East Troy, WI 53120

shopuriel.com Lot: